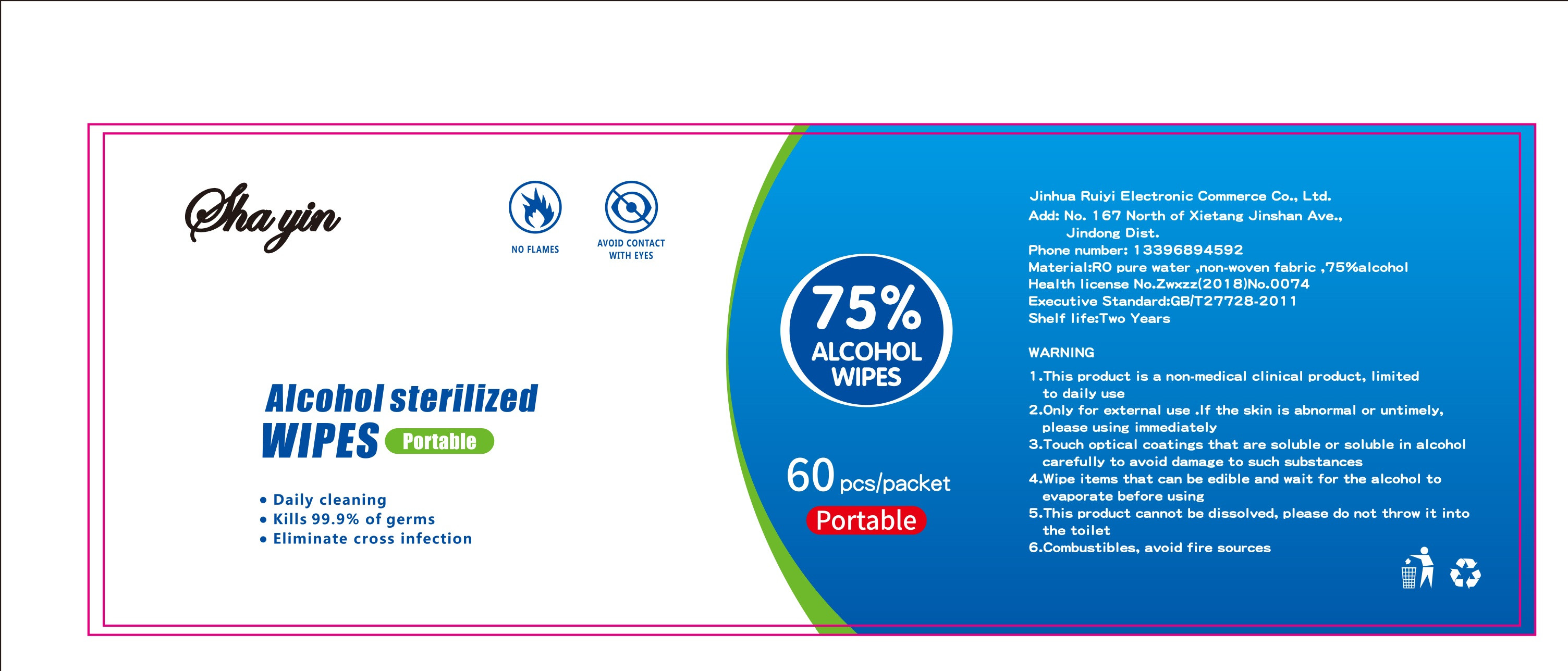 DRUG LABEL: Alcohol sterilized wipes
NDC: 68765-001 | Form: CLOTH
Manufacturer: Jinhua Ruiyi Electronic Commerce Co., Ltd.
Category: otc | Type: HUMAN OTC DRUG LABEL
Date: 20200605

ACTIVE INGREDIENTS: ALCOHOL 140 mL/60 1
INACTIVE INGREDIENTS: WATER

DOSAGE AND ADMINISTRATION

Store in a cool and dry place

INACTIVE INGREDIENT

Ro pure water

Non-woven fabric

INDICATIONS AND USAGE

Lift the packet, tear off the tape and pull out the wet wipes.After use, please close the sealing flap in time to avoid internal water evaporation.Then wipe the surface of the object with wipes until dry.

ACTIVE INGREDIENT

Alcohol

keep out of reach of children

PURPOSE

Disinfection
Sterilization
No Rinseing

WARNINGS

1.This product is a non-medical clinical product, limited to daily use
2.Only for external use .If the skin is abnormal or untimely,please using immediately
3.Touch optical coatings that are soluble or soluble in alcohol carefully to avoid damage to such substances
4.Wipe items that can be edible and wait for the alcohol to evaporate before using
5.This product cannot be dissolved, please do not throw it into the toilet
6.Combustibles, avoid fire sources